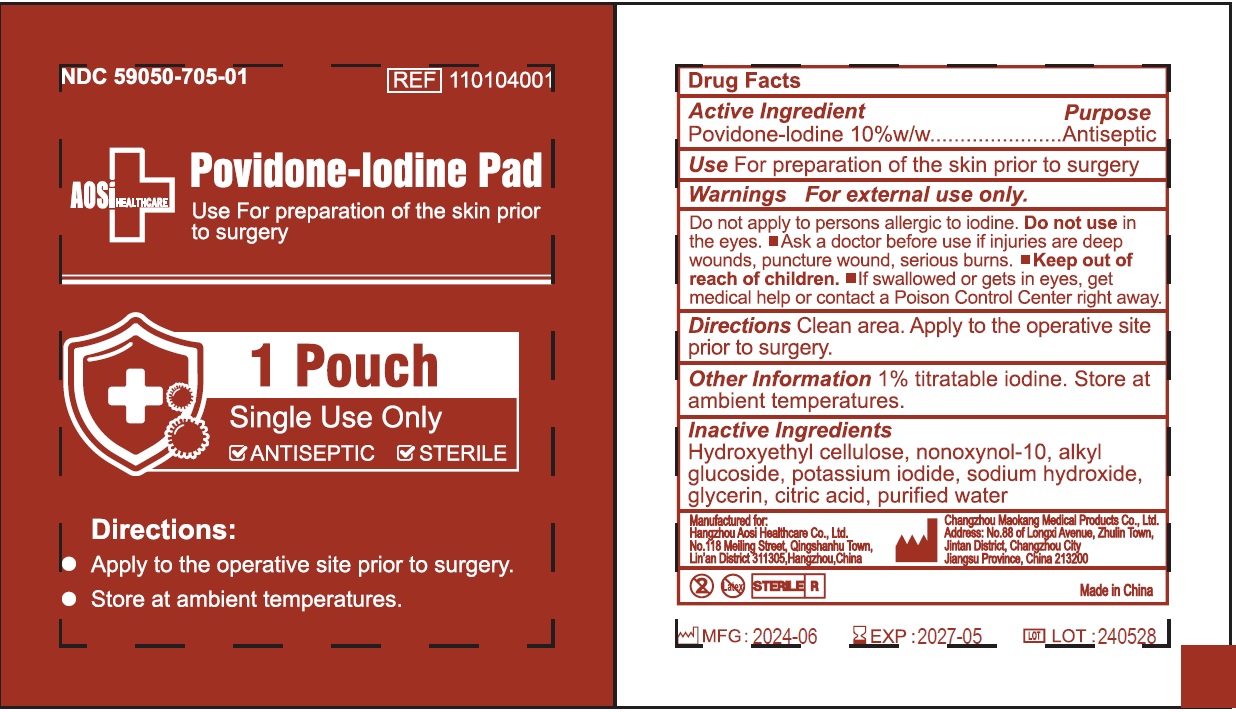 DRUG LABEL: Povidone Iodine Pad
NDC: 59050-705 | Form: LIQUID
Manufacturer: Changzhou Maokang Medical Products Co., Ltd
Category: otc | Type: HUMAN OTC DRUG LABEL
Date: 20241121

ACTIVE INGREDIENTS: POVIDONE-IODINE 100 mg/1 g
INACTIVE INGREDIENTS: HYDROXYETHYL CELLULOSE, UNSPECIFIED; NONOXYNOL-10; POTASSIUM IODIDE; SODIUM HYDROXIDE; GLYCERIN; CITRIC ACID MONOHYDRATE; WATER

Povidone-Iodine Pad

Active Ingredient

Povidone-Iodine 10%w/w

Purpose

Antiseptic

Use

For preparation of the skin prior to surgery

Warnings

For external use only.

Do not apply to persons allergic to iodine.

Do not use

in the eyes.

Ask a doctor before use

if injuries are deep wounds, puncture wound, serious burns.

• Keep out of reach of children.

- If swallowed or gets in eyes, get medical help, or contact a Poison Control Center right away.

Directions

Clean area. Apply to the operative site prior to surgery.

Other Information

1% titratable iodine. Store at ambient temperatures.

Inactive ingredients

Hydroxyethyl cellulose, nonoxynol-10, alkyl glucoside, potassium iodide, sodium hydroxide, glycerin, citric acid, purified water